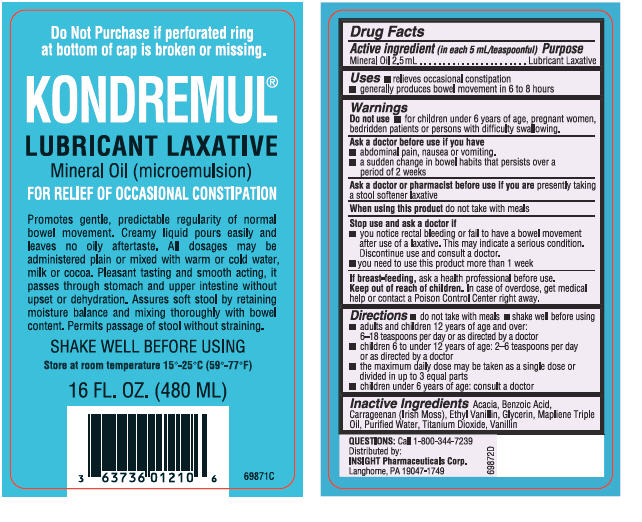 DRUG LABEL: Kondremul
NDC: 63736-012 | Form: LIQUID
Manufacturer: Insight Pharmaceuticals
Category: otc | Type: HUMAN OTC DRUG LABEL
Date: 20100111

ACTIVE INGREDIENTS: Mineral Oil 2.5 mL/5 mL
INACTIVE INGREDIENTS: Water; Acacia; Glycerin; Benzoic Acid; Titanium Dioxide

KONDREMUL®
LUBRICANT LAXATIVE

Drug Facts

Active ingredient (in each 5 mL/teaspoonful)

Mineral Oil 2.5 mL

Purpose

Lubricant Laxative

Uses

- relieves occasional constipation
- generally produces bowel movement in 6 to 8 hours

Warnings

Do not use

- for children under 6 years of age, pregnant women, bedridden patients or persons with difficulty swallowing.

Ask a doctor before use if you have

- abdominal pain, nausea or vomiting.
- a sudden change in bowel habits that persists over a period of 2 weeks

Ask a doctor or pharmacist before use if you are presently taking a stool softener laxative

When using this product do not take with meals

Stop use and ask a doctor if

- you notice rectal bleeding or fail to have a bowel movement after use of a laxative. This may indicate a serious condition. Discontinue use and consult a doctor.
- you need to use this product more than 1 week

PREGNANCY OR BREAST FEEDING

If breast-feeding, ask a health professional before use.

Keep out of reach of children. In case of overdose, get medical help or contact a Poison Control Center right away.

Directions

- do not take with meals
- shake well before using
- adults and children 12 years of age and over:
  6–18 teaspoons per day or as directed by a doctor
- children 6 to under 12 years of age:
  2–6 teaspoons per day or as directed by a doctor
- the maximum daily dose may be taken as a single dose or divided in up to 3 equal parts
- children under 6 years of age: consult a doctor

Inactive Ingredients

Acacia, Benzoic Acid, Carrageenan (Irish Moss), Ethyl Vanillin, Glycerin, Mapliene Triple Oil, Purified Water, Titanium Dioxide, Vanillin

QUESTIONS

Call 1-800-344-7239

Distributed by:
INSIGHT Pharmaceuticals Corp.
Langhorne, PA 19047-1749

PRINCIPAL DISPLAY PANEL - 480 mL Bottle Label

Do Not Purchase if perforated ring
at bottom of cap is broken or missing.

KONDREMUL®
LUBRICANT LAXATIVE

Mineral Oil (microemulsion)

FOR RELIEF OF OCCASIONAL CONSTIPATION

Promotes gentle, predictable regularity of normal
bowel movement. Creamy liquid pours easily and
leaves no oily aftertaste. All dosages may be
administered plain or mixed with warm or cold water,
milk or cocoa. Pleasant tasting and smooth acting, it
passes through stomach and upper intestine without
upset or dehydration. Assures soft stool by retaining
moisture balance and mixing thoroughly with bowel
content. Permits passage of stool without straining.

SHAKE WELL BEFORE USING

Store at room temperature 15°-25°C (59°-77°F)

16 FL. OZ. (480 ML)

69871C